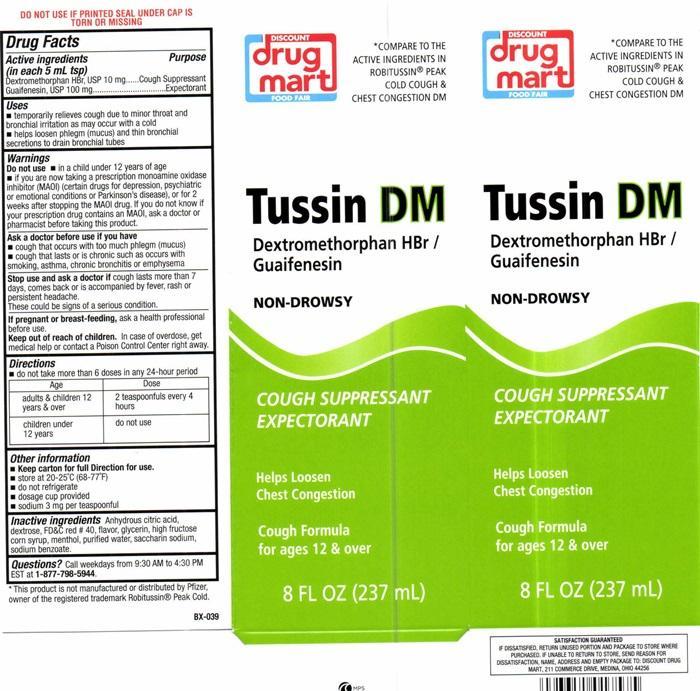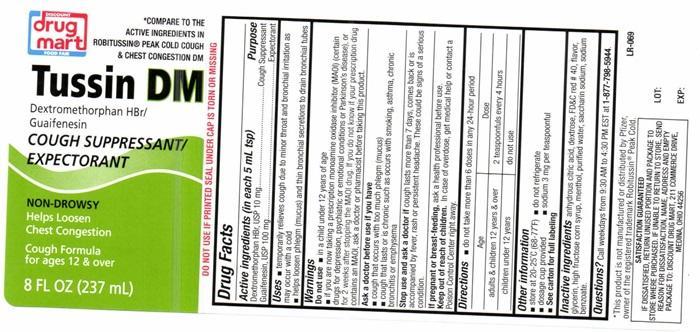 DRUG LABEL: Tussin DM
NDC: 53943-503 | Form: LIQUID
Manufacturer: Discount Drug Mart
Category: otc | Type: HUMAN OTC DRUG LABEL
Date: 20251223

ACTIVE INGREDIENTS: DEXTROMETHORPHAN HYDROBROMIDE 10 mg/5 mL; GUAIFENESIN 100 mg/5 mL
INACTIVE INGREDIENTS: ANHYDROUS CITRIC ACID; DEXTROSE; FD&C RED NO. 40; HIGH FRUCTOSE CORN SYRUP; MENTHOL; WATER; SACCHARIN SODIUM; SODIUM BENZOATE

Drug Facts Active ingredients (in each 5 mL tsp)

Dextromethorphan HBr, USP 10 mg

Guaifenesin, USP 100 mg

Purpose

Cough Suppressant

Expectorant

Keep out of reach of children. In case of overdose, get medical help or contact a Poison Control Center right away.

Uses

- temporarily relieves cough due to minor throat and bronchial irritation as may occur with a cold
- helps loosen phlegm (mucus) and thin bronchial secretions to drain bronchial tubes

Warnings

DO NOT USE IF PRINTED SEAL UNDER CAP IS TORN OR MISSING.

Do not use

- in a child under 12 years of age
- if you are now taking a prescription monoamine oxidase inhibitor (MAOI) (certain drugs for depression, psychiatric or emotional conditions or Parkinson's disease), or for 2 weeks after stopping the MAOI drug. If you do not know if your prescription drug contains an MAOI, ask a doctor or pharmacist before taking this product.

Ask a doctor before taking if you have

- cough that occurs with too much phlegm (mucus)
- cough that lasts or is chronic such as occurs with smoking, asthma, bronchitis or emphysema

Stop use and ask a doctor if

cough lasts more than 7 days, comes back or is accompanied by fever, rash or persistant headache.

These could be signs of a serious condition.

If pregnant or breast-feeding,

ask a health professional before use.

Directions

- do not take more than 6 doses in any 24-hour period

Age | Dose
Adults and children 12 years and over | 2 teaspoonfuls every 4 hours
chilldren under 12 years | do not use

Other information

- Keep carton for full Direction for use.
- store at 20°-25°C (68°-77°F)
- do not refrigerate
- dosage cup provided
- sodium 3 mg per teaspoonful

Inactive ingredients

Anhydrous citric acid, dextrose, FD and red # 40, flavor, glycerin, high fructose corn syrup, menthol, purified water, saccharin sodium, sodium benzoate.

Questions?

Call weekdays from 9:30 AM to 4:30 PM EST at 1-877-798-5944

DISCOUNT drug mart FOOD FAIR Tussin DM product label

*COMPARE TO THE ACTIVE INGREDIENTS IN ROBITUSSIN® PEAK COLD COUGH AND CHEST CONGESTION DM

DISCOUNT

drug mart

FOOD FAIR

Tussin DM

Dextromethorphan HBr/ Guaifenesin

NON-DROWSY

COUGH SUPPRESSANT

EXPECTORANT

Helps Loosen

Chest Congestion

Cough Formula

for ages 12 & over

8 FL OZ (237 mL)

* This product is not manufactured or distributed bynPfizer, owner of the registered trademark Robitussin® Peak Cold.

BX-039

SATISFACTION GUARANTEED
IF DISSASIFIED , RETURN UNUSED PORTION AND PACKAGE TO STORE WHERE PURCHASED. IF UNABLE TO RETURN TO STORE, SEND REASON FOR DISSATISFACTION, NAME, ADDRESS AND EMPTY PACKAGE TO: DISCOUNT DRUG MART, 211 COMMERCE DRIVE, MEDINA, OHIO 44256

res